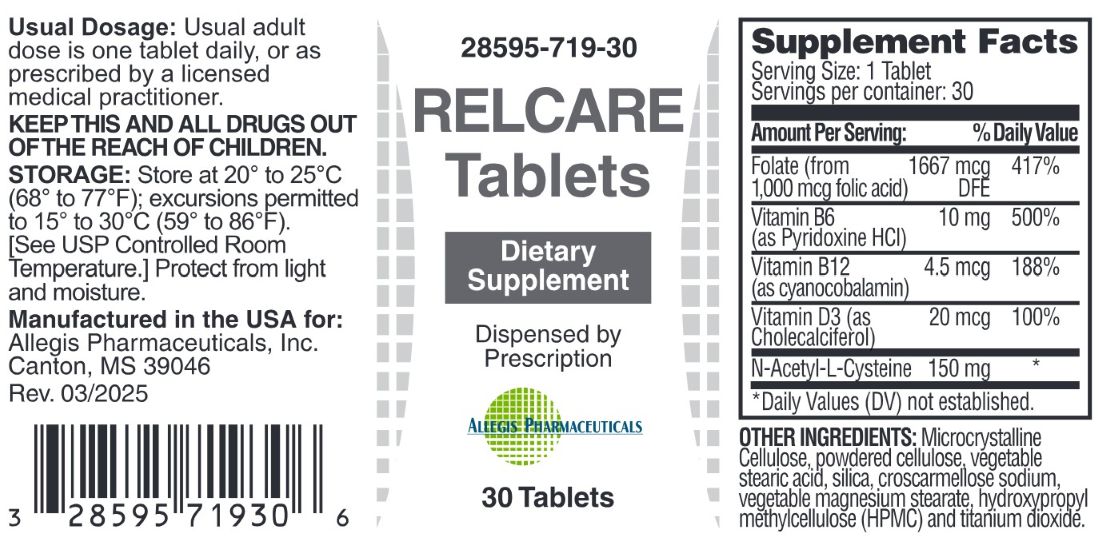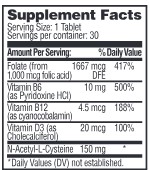 DRUG LABEL: Relcare
NDC: 28595-719 | Form: TABLET, COATED
Manufacturer: Allegis Pharmaceuticals, LLC
Category: other | Type: DIETARY SUPPLEMENT
Date: 20250416

ACTIVE INGREDIENTS: CYANOCOBALAMIN 4.5 ug/1 1; N-ACETYL-L-CYSTEINE 2-DEOXY-3-THIO-D-ERYTHRO-PENTONIC ACID .GAMMA.-LACTONE THIOETHER 150 mg/1 1; CHOLECALCIFEROL 20 ug/1 1; PYRIDOXINE HYDROCHLORIDE 10 mg/1 1; FOLIC ACID 1667 ug/1 1
INACTIVE INGREDIENTS: CELLULOSE, MICROCRYSTALLINE; POWDERED CELLULOSE; STEARIC ACID; SILICA; CROSCARMELLOSE SODIUM; TITANIUM DIOXIDE; MAGNESIUM STEARATE; HYDROXYPROPYL METHYLCELLULOSE

Relcare Tablets

Suplement Facts

Other Ingredients:

Microcrystalline cellulose, powder cellulose,vegetable stearic acid, silica, croscarmellose sodium, vegetable megnesium stearate, hydroxypropyl methylcellulose (HPMC), titanium oxide.

Precautions

Folic acid alone is improper therapy in the treatment of pernicious anemia and other megaloblastic anemias where vitamine B12 is deficient.

Folic acid in doses above 0.1 mg daily may obscure pernicious anemia in that hematologic remission can occur while neurological manifestations progress. Relcare Tablets should only be used under the direction and supervision of a licensed medical practitioner.

Contraindications

Relcare Tablets are contraindicated in patients with a know hypersensitivity to any of the contained ingredients. Do not take this product if you are presently taking mineral oil, unless directed by a licensed medical practitioner.

Warnings

KEEP THIS AND ALL DRUGS OUT OF THE REACH OF CHILDREN.

In case of accidental overdose, call a licensed medical practitioner or poison control center immediately.

For use under the supervision of a licensed medical practitioner.

Dispense in a tight, light resistant container as defined in the USP/NF in a child-resistant closure.

Adverse Reactions

Allergic sensitization has been reported following both oral and parenteral administration of folic acid. You may report side effects by calling Allegis Pharmaceuticals at 1-866-633-9033 or the FDA by calling 1-800-FDA-1088

Dosage and Adminstration

Description: Relcare Tablets is a prescription dietary supplement intended for oral adminstration.

Indication and Usage: Relcare Tablets is to privide significant amounts of Vitamins B6, B12, D3, and folate to supplement the diet, and to help assure that nutritional deficiencies of these vitaines will not develop.

Dosage: Usual adult dose is one tablet daily, or as prescribed by a licensed medical practitioner.

Storage

Store at 20° to 25°C (68° to 77°F); excursions permitted to 15° to 30°C (59° to 86°F). [See USP Controlled Room Temperature.] Protect from light and moisture.Tamper Evident: Do not use if seal if broken or missing.

Statements

† This product is a prescription-folate with or without other dietary ingredients that – due to increased folate levels increased risk associated with masking of B12 deficiency (pernicious anemia) requires administration under the care of a licensed medical practitioner (61 FR 8760). 1-3 The most appropriate way to ensure pedigree reporting consistent with these regulatory guidelines and safety monitoring is to dispense this product only by prescription. This is not an Orange Book product. This product may be administered only under a physician’s supervision and all prescriptions using this product shall be pursuant to state statutes as applicable.

The ingredients, indication or claims of this product are not to be construed to be drug claims.

1. Federal Register Notice of August 2, 1973 (38 FR20750) 2. Federal Register Notice of October 17, 1980 (45 FR69043, 69044) 3. Federal Register Notice of March 5, 1996 (61 FR 8760)

How Supplied

Relcare Tablets: Each bottle contains 30 tablets (white) (28595-719-30)

Relcare Tablets are avaiable as white, round tablets with F100 imprint and are available in 30 count bottles (28595-719-30)

These Statements have note been evaluated by the FDA. This product is not intended to diagnose, treat, cure, or prevent any disease.

Manufactured in the USA for:

Allegis Pharmaceuticals, LLC

Canton, MS 39046

Rev 03/2025